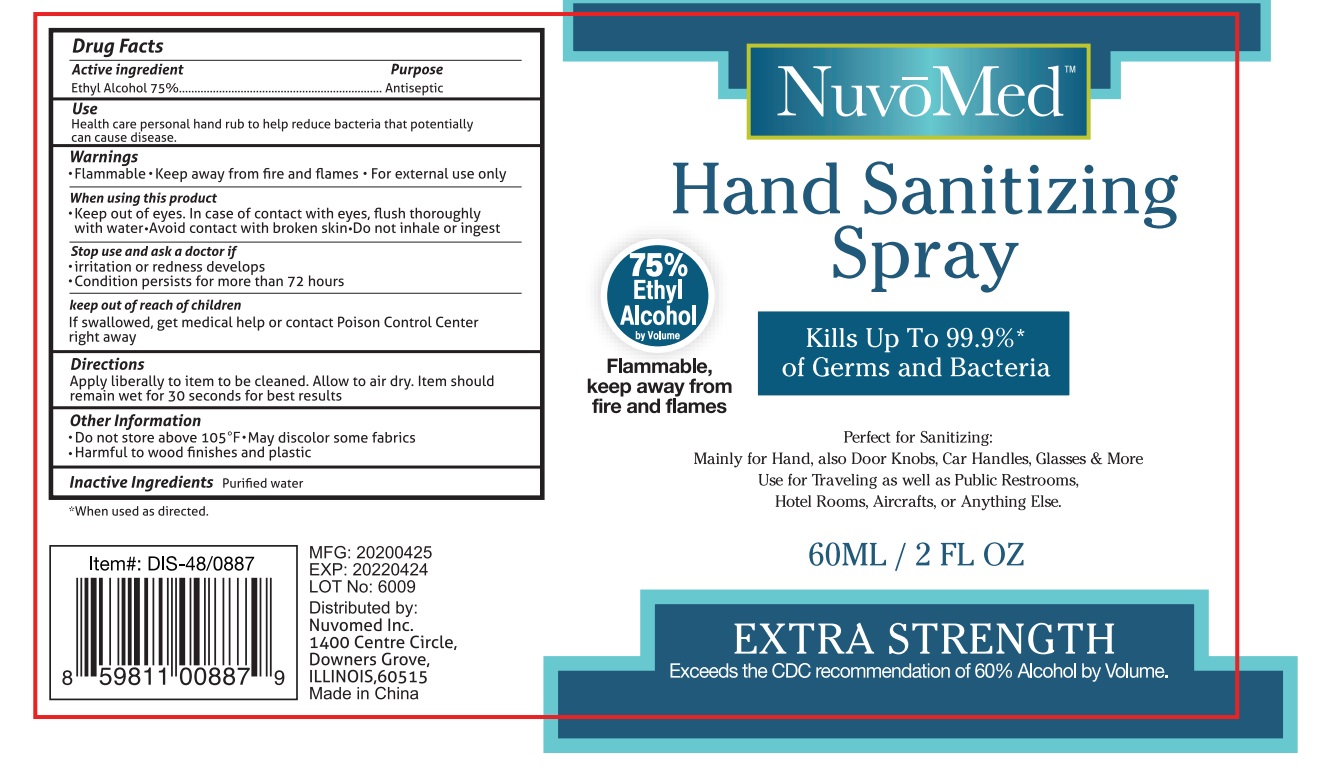 DRUG LABEL: Nuvo Med Hand Sanitizer
NDC: 74542-005 | Form: SPRAY
Manufacturer: Ningbo SKL International Co.,Ltd.
Category: otc | Type: HUMAN OTC DRUG LABEL
Date: 20200421

ACTIVE INGREDIENTS: ALCOHOL 75 mL/100 mL
INACTIVE INGREDIENTS: WATER

Active Ingredient

Ethyl Alcohol 75% v/v.

Purpose

Antiseptic

Use

Personal hand rub to help reuce bacteria that potentially can use.

Warnings

For external use only
Flammable
Keep away from fire or flame

When using this product:
Keep out of eyes. In case of contact with eyes, flush thoroughly with water.
Avoid contact with broken skin.
Do not inhale or ingest.

Stop use and ask a doctor if:
Irritation or redness develops
Condition persists for more than 72 hours.

Other Information
Do not store above 105℉
May discolor some fabrics
Harmful to wood finishes and plastics

Keep out of reach of children

If swallowed, get medical help or contact a Poison Control Center right away

Directions

- Place enough product on hand to cover all surfaces. Rub hands together until dry.
- Supervise children under 6 years of age when using this product to avoid swallowing.

Inactive ingredients

Purified water